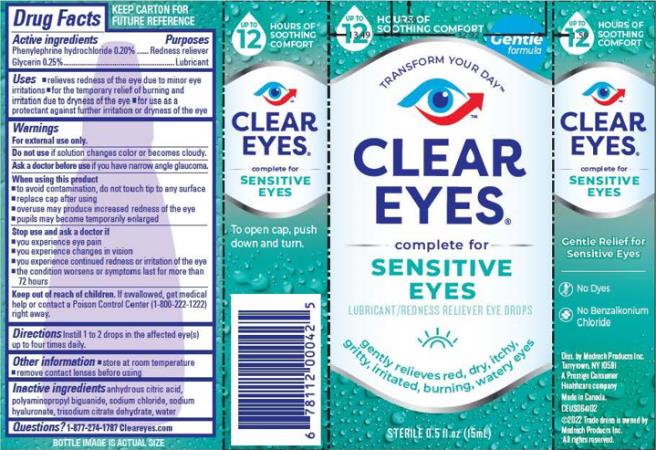 DRUG LABEL: Clear Eyes Sensitive
NDC: 67172-503 | Form: SOLUTION/ DROPS
Manufacturer: Prestige Brands Holdings, Inc.
Category: otc | Type: HUMAN OTC DRUG LABEL
Date: 20240401

ACTIVE INGREDIENTS: PHENYLEPHRINE HYDROCHLORIDE 2 mg/1 mL; GLYCERIN 2.5 mg/1 mL
INACTIVE INGREDIENTS: ANHYDROUS CITRIC ACID; POLYAMINOPROPYL BIGUANIDE; SODIUM CHLORIDE; HYALURONATE SODIUM; TRISODIUM CITRATE DIHYDRATE; WATER

Clear eyes Sensitive

Drug Facts

Active ingredients

Phenylephrine hydrochloride 0.20%

Glycerin 0.25%

Purposes

Redness reliever

Lubricant

Uses

- relieves redness of the eye due to minor eye irritations
- for the temporary relief of burning and irritation due to dryness of the eye
- for use as a protectant against further irritation or dryness of the eye

Warnings

For external use only

Do not use

if solution changes color or becomes cloudy

Ask a doctor before use if you have

narrow angle glaucoma

When using this product

- to avoid contamination, do not touch tip to any surface
- replace cap after using
- overuse may produce increased redness of the eye
- pupils may become temporarily enlarged

Stop use and ask a doctor if

- you experience eye pain
- you experience changes in vision
- you experience continued redness or irritation of the eye
- the condition worsens or symptoms last for more than 72 hours

Keep out of reach of children.

If swallowed, get medical help or contact a Poison Control Center (1-800-222-1222) right away

Ask a doctor before use if you have

narrow angle glaucoma

Directions

Instill 1 to 2 drops in the affected eye(s) up to four times daily

Other information

- store at room temperature
- remove contact lenses before using

Inactive ingredients

anhydrous citric acid, polyaminopropyl biguanide, sodium chloride, sodium hyaluronate, trisodium citrate dehydrate, water

Questions?

1-877-274-1787 Cleareyes.com

PRINCIPAL DISPLAY PANEL

CLEAR EYES®

complete for
SENSITIVE EYES

LUBRICANT/REDNESS RELIEVER EYE DROPS

STERILE 0.5 FL OZ (15 mL)